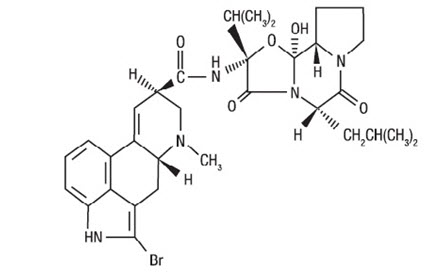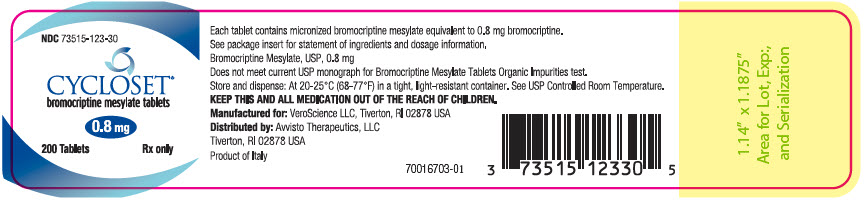 DRUG LABEL: CYCLOSET
NDC: 73515-123 | Form: TABLET
Manufacturer: Avvisto Therapeutics LLC
Category: prescription | Type: HUMAN PRESCRIPTION DRUG LABEL
Date: 20260112

ACTIVE INGREDIENTS: bromocriptine mesylate 0.8 mg/1 1
INACTIVE INGREDIENTS: lactose, unspecified form; starch, corn; magnesium stearate; silicon dioxide; citric acid monohydrate

HIGHLIGHTS OF PRESCRIBING INFORMATION

These highlights do not include all the information needed to use CYCLOSET safely and effectively. See full prescribing information for CYCLOSET.
CYCLOSET® (bromocriptine mesylate tablets), for oral use
Initial U.S. Approval: 1978

RECENT MAJOR CHANGES

Warnings and Precautions (5.3) | 04/2020
Warnings and Precautions (5.7) | 08/2020

1 INDICATIONS AND USAGE

CYCLOSET is an ergot derivative indicated as an adjunct to diet and exercise to improve glycemic control in adults with type 2 diabetes mellitus. (1)

Limitations of Use:

- Should not be used to treat type 1 diabetes or diabetic ketoacidosis. (1)
- Limited efficacy data in combination with thiazolidinediones. (1)
- Efficacy has not been confirmed in combination with insulin. (1)

2 DOSAGE AND ADMINISTRATION

- Taken within two hours after waking in the morning with food (2.1)
- Initial dose is one tablet (0.8 mg) daily increased weekly by one tablet until maximal tolerated daily dose of 1.6 to 4.8 mg is achieved. (2.2)
- Limit dose to 1.6 mg daily during concomitant use of a moderate CYP3A4 inhibitor. Avoid concomitant use with strong CYP3A4 inhibitors. (2.3)

3 DOSAGE FORMS AND STRENGTHS

Tablets: 0.8 mg (3)

4 CONTRAINDICATIONS

- Hypersensitivity to ergot-related drugs, bromocriptine or to any of the excipients in CYCLOSET. (4)
- History of syncopal migraines. (4)
- Postpartum patients (4, 5.7)
- Lactating patients (4, 8.2)

5 WARNINGS AND PRECAUTIONS

- Hypotension: Can cause orthostatic hypotension and syncope, particularly upon initiation or dose escalation. Use caution in patients taking antihypertensive medications. Assess orthostatic vital signs prior to initiation of CYCLOSET and periodically thereafter. Advise patients during early treatment to avoid situations that could lead to injury if syncope was to occur. (5.1, 6.1)
- Psychosis: May exacerbate psychotic disorders or reduce the effectiveness of drugs that treat psychosis. Use in patients with severe psychotic disorders is not recommended. (5.2)
- Impulse control/compulsive behaviors: Ask patients or their caregivers about new or increased gambling urges, sexual urges, uncontrolled spending, or other urges while being treated with CYCLOSET. Consider dose reduction or stopping CYCLOSET if a patient develops such urges. Use of CYCLOSET in patients with impulse control/compulsive behaviors is not recommended. (5.3, 6.2).
- Somnolence: May cause somnolence. Advise patients not to operate heavy machinery if symptoms of somnolence occur. (5.4)
- Interaction with dopamine antagonists: Concomitant use with dopamine antagonists such as neuroleptic agents may diminish the effectiveness of both drugs. Concomitant use is not recommended. (5.5, 7)
- Other dopamine receptor agonists: Effectiveness and safety are unknown in patients already taking dopamine receptor agonists for other indications. Concomitant use is not recommended. (5.6)
- Risks in Postpartum Patients: Serious and life-threatening adverse reactions have been reported. (5.7, 6.2)

6 ADVERSE REACTIONS

In controlled clinical trials, adverse reactions reported in ≥5% of patients treated with CYCLOSET and reported more commonly than in patients treated with placebo, included nausea, fatigue, dizziness, vomiting, and headache. (6.1)

Postmarketing reports with higher doses of bromocriptine used for other indications include psychotic disorders, hallucinations, and fibrotic complications. (6.2)

To report SUSPECTED ADVERSE REACTIONS, contact VeroScience, LLC at 1-888-621-1215 or FDA at 1-800-FDA-1088 or www.fda.gov/medwatch.

7 DRUG INTERACTIONS

- May increase the unbound fraction of highly protein-bound therapies, altering their effectiveness and safety profiles. (7)
- May increase ergot-related side effects or reduce ergot effectiveness for migraines if co-administered within 6 hours of ergot-related drugs. (7)
- Extensively metabolized by CYP3A4. Limit CYCLOSET dose to 1.6 mg/day during concomitant use of moderate CYP3A4 inhibitors. Avoid concomitant use of CYCLOSET with strong CYP3A4 inhibitors. (2.3, 7)

8 USE IN SPECIFIC POPULATIONS

Pediatrics: Safety and effectiveness have not been established. (8.4)

FULL PRESCRIBING INFORMATION

1 INDICATIONS AND USAGE

CYCLOSET is indicated as an adjunct to diet and exercise to improve glycemic control in adults with type 2 diabetes mellitus.

Limitations of Use

- CYCLOSET should not be used to treat type 1 diabetes or diabetic ketoacidosis.
- Limited efficacy data in combination with thiazolidinediones.
- Efficacy has not been confirmed in combination with insulin.

2 DOSAGE AND ADMINISTRATION

2.1 Recommended Dosing

The recommended dose of CYCLOSET is 1.6 mg to 4.8 mg administered once daily within two hours after waking in the morning. CYCLOSET should be taken with food to potentially reduce gastrointestinal side effects such as nausea. If the morning dose is missed, instruct patients to take their usual dose the following morning. Doses of CYCLOSET should not be doubled the following morning.

2.2 Titration

CYCLOSET should be initiated at one tablet (0.8 mg) and increased by one tablet per week until a maximum daily dose of 6 tablets (4.8 mg) or until the maximal tolerated number of tablets between 2 and 6 per day is reached.

2.3 Use with Concomitant Therapy

CYCLOSET dose should not exceed 1.6 mg once daily during concomitant use of a moderate CYP3A4 inhibitor (e.g., erythromycin). Avoid concomitant use of CYCLOSET and strong CYP3A4 inhibitors (e.g., azole antimycotics, HIV protease inhibitors) and ensure adequate washout of the strong CYP3A4 inhibitor drug before initiating CYCLOSET treatment [see Drug Interactions (7), Clinical Pharmacology (12.3)].

3 DOSAGE FORMS AND STRENGTHS

0.8 mg tablets are white and round, imprinted with "C" on one side and "9" on the other.

4 CONTRAINDICATIONS

CYCLOSET is contraindicated in:

- Patients with known hypersensitivity to bromocriptine, ergot-related drugs, or any of the excipients in CYCLOSET.
- Patients with syncopal migraine. Bromocriptine increases the likelihood of a hypotensive episode among patients with syncopal migraine. Loss of consciousness during a migraine may reflect dopamine receptor hypersensitivity. CYCLOSET is a dopamine receptor agonist and may, therefore, potentiate the risk for syncope in these patients.
- Postpartum patients. Serious and life-threatening adverse reactions have been reported with bromocriptine use in this population [see Warnings and Precautions (5.7), Adverse Reactions (6.2)].
- Lactating patients. CYCLOSET contains bromocriptine which inhibits lactation [see Use in Specific Populations (8.2)].

5 WARNINGS AND PRECAUTIONS

5.1 Hypotension

Hypotension, including orthostatic hypotension, can occur, particularly upon initiation of CYCLOSET therapy and with dose escalation. In a 52-week, randomized clinical trial of 3070 patients, hypotension was reported in 2.2% of patients randomized to CYCLOSET compared to 0.8% of patients randomized to placebo. Among CYCLOSET-treated patients reporting symptomatic hypotension, 98% were on at least one blood pressure medication compared to 73% on such medication in the total study population. In this trial, six CYCLOSET-treated patients (0.3%) reported orthostatic hypotension compared to 2 (0.2%) placebo-treated patients. All six patients were taking antihypertensive medications. Hypotension can result in syncope. In this trial, syncope due to any cause was reported in 1.6% of CYCLOSET-treated patients and 0.7% of placebo-treated patients [see Adverse Reactions (6.1)]. As a precaution, assessment of orthostatic vital signs is recommended prior to initiation of CYCLOSET and periodically thereafter. Advise patients during early treatment with CYCLOSET to make slow postural changes and to avoid situations that could lead to serious injury if syncope was to occur. Use caution in patients taking antihypertensive medications.

5.2 Psychotic Disorders

In patients with severe psychotic disorders, treatment with a dopamine receptor agonist such as CYCLOSET may exacerbate the disorder or may diminish the effectiveness of drugs used to treat the disorder. Therefore, the use of CYCLOSET in patients with severe psychotic disorders is not recommended.

5.3 Impulse Control/Compulsive Behaviors

There have been reports of patients experiencing intense urges to gamble, increased sexual urges, intense urges to spend money uncontrollably, and/or other intense urges, and the inability to control these urges while taking one or more of the medications, including bromocriptine, that increase central dopaminergic tone. In some cases, although not all, these urges were reported to have stopped when the dose was reduced, or the medication was discontinued. Because patients may not recognize these behaviors as abnormal, it is important to specifically ask patients or their caregivers about the development of new or increased gambling urges, sexual urges, uncontrolled spending, or other urges while being treated with CYCLOSET. Consider dose reduction or discontinuation if a patient develops such urges.

5.4 Somnolence

CYCLOSET may cause somnolence. In a 52-week, randomized clinical trial, 4.3% of CYCLOSET-treated patients and 1.3% of placebo-treated patients reported somnolence. None of these events were reported as serious, and the majority of patients reported resolution of somnolence over time. Inform patients of the risk of somnolence, particularly when initiating therapy with CYCLOSET. Patients experiencing somnolence should refrain from driving or operating heavy machinery.

5.5 Interaction with Dopamine Receptor Antagonists

Dopamine receptor antagonists, including neuroleptic agents that have dopamine D2 receptor antagonist properties (e.g., clozapine, olanzapine, ziprasidone), may reduce the effectiveness of CYCLOSET, and CYCLOSET may reduce the effectiveness of these agents. CYCLOSET has not been studied in patients taking neuroleptic drugs. The concomitant use of CYCLOSET and dopamine receptor antagonists, including neuroleptic drugs, is not recommended.

5.6 Other Dopamine Receptor Agonists

Other dopamine receptor agonists are indicated for the treatment of Parkinson's disease, hyperprolactinemia, restless leg syndrome, acromegaly, and other disorders. The effectiveness and safety of CYCLOSET in patients who are already taking one of these other dopamine receptor agonists is unknown. Concomitant use is not recommended.

5.7 Risks in Postpartum Patients

CYCLOSET is contraindicated in postpartum patients. Serious and life-threatening adverse reactions including hypertension, myocardial infarction, seizures, stroke and psychosis have been reported postmarketing in postpartum women who were administered bromocriptine for inhibition of lactation [see Adverse Reactions (6.2)]. These risks may be higher in postpartum patients with cardiovascular disease. The indication for use of bromocriptine for inhibition of postpartum lactation was withdrawn from bromocriptine-containing products and is not approved for CYCLOSET.

6 ADVERSE REACTIONS

The following clinically significant adverse reactions are described elsewhere in the labeling:

- Hypotension [see Warnings and Precautions (5.1)]
- Psychotic Disorders [see Warnings and Precautions (5.2)]
- Somnolence [see Warnings and Precautions (5.4)]
- Risks in Postpartum Women [see Warnings and Precautions (5.7)]

6.1 Clinical Trials Experience

Because clinical trials are conducted under widely varying conditions, the adverse reaction rates reported in one clinical trial may not be easily compared to those rates reported in another clinical trial and may not reflect the rates actually observed in clinical practice.

The CYCLOSET safety trial was a 52-week, placebo-controlled study. A total of 3,070 patients were randomized to CYCLOSET (titrated to 1.6 to 4.8 mg daily, as tolerated) or placebo. The study population had a mean baseline age of 60 years (range 27-80) and 33% were 65 years of age or older. Approximately 43% of the patients were female, 68% were Caucasian, 17% were Black, 13% were Hispanic, and 1% were Asian. The mean baseline body mass index was 32 kg/m^2. The mean duration of diabetes at baseline was 8 years, and the mean baseline HbA1c was 7.0% with a mean baseline fasting plasma glucose of 142 mg/dL. At baseline, 12% of patients were treated with diet only, 40% were treated with one oral antidiabetic agent, 33% were treated with two oral antidiabetic agents, and 16% were treated with insulin alone or insulin in combination with an oral antidiabetic agent. At baseline, 76% of patients reported a history of hypercholesterolemia, 75% reported a history of hypertension, 11% reported a history of revascularization surgery, 10% reported a history of myocardial infarction, 10% reported a history of angina, and 5% reported a history of stroke. Forty-seven percent of the CYCLOSET-treated patients and 32% of the placebo-treated patients prematurely discontinued treatment.

Table 1 summarizes the adverse reactions reported in ≥5% of patients treated with CYCLOSET in clinical trials regardless of investigator assessment of causality. The most commonly reported adverse reactions (nausea, fatigue, vomiting, headache, dizziness) lasted a median of 14 days and were more likely to occur during the initial titration of CYCLOSET. There were no differences in the pattern of common adverse reactions across race groups or age groups (<65 years old vs. >65 years old). In the 52-week CYCLOSET safety trial, 11.5% of CYCLOSET-treated women compared to 3.6% of placebo-treated women reported vomiting. In this same trial, 5.4% of CYCLOSET-treated men compared to 2.8% of placebo-treated men reported vomiting.

Table 1: Adverse Reactions Occurring in ≥5% in CYCLOSET-Treated Patients and More Frequent than in Placebo in CYCLOSET Clinical Trials [All randomized subjects receiving at least one dose of study drug]
Monotherapy | CYCLOSET 1.6 mg – 4.8 mg N (%) | Placebo N (%)
N = 159 | N = 80 | N = 79
Nausea | 26 (32.5) | 6 (7.6)
Rhinitis | 11 (13.8) | 3 (3.8)
Headache | 10 (12.5) | 7 (8.9)
Asthenia | 10 (12.5) | 5 (6.3)
Dizziness | 10 (12.5) | 6 (7.6)
Constipation | 9 (11.3) | 3 (3.8)
Sinusitis | 8 (10.0) | 2 (2.5)
Diarrhea | 7 (8.8) | 4 (5.1)
Amblyopia | 6 (7.5) | 1 (1.3)
Dyspepsia | 6 (7.5) | 2 (2.5)
Vomiting | 5 (6.3) | 1 (1.3)
Infection | 5 (6.3) | 4 (5.1)
Anorexia | 4 (5.0) | 1 (1.3)
Adjunct to Sulfonylurea (2 pooled 24-week studies)
N = 494 | N = 244 | N = 250
Nausea | 62 (25.4) | 12 (4.8)
Asthenia | 46 (18.9) | 20 (8.0)
Headache | 41 (16.8) | 40 (16.0)
Flu syndrome | 23 (9.4) | 19 (7.6)
Constipation | 24 (9.8) | 11 (4.4)
Cold | 20 (8.2) | 20 (8.0)
Dizziness | 29 (11.9) | 14 (5.6)
Rhinitis | 26 (10.7) | 12 (4.8)
Sinusitis | 18 (7.4) | 16 (6.4)
Somnolence | 16 (6.6) | 5 (2.0)
Vomiting | 13 (5.3) | 8 (3.2)
Amblyopia | 13 (5.3) | 6 (2.4)
52-Week Safety Trial [The Safety Trial enrolled patients treated with diet or no more than 2 antidiabetic medications (metformin, insulin secretagogues such as a sulfonylurea, thiazolidinediones, alpha glucosidase inhibitors, and/or insulin).]
N = 3070 | N = 2054 | N = 1016
Nausea | 661 (32.2) | 77 (7.6)
Dizziness | 303 (14.8) | 93 (9.2)
Fatigue | 285 (13.9) | 68 (6.7)
Headache | 235 (11.4) | 84 (8.3)
Vomiting | 167 (8.1) | 32 (3.1)
Diarrhea | 167 (8.1) | 81 (8.0)
Constipation | 119 (5.8) | 52 (5.1)

Hypoglycemia

In the monotherapy trial, hypoglycemia, a blood glucose level of less than 60 mg/dL, was reported in 2 CYCLOSET-treated patients (3.7%) and 1 placebo-treated patient (1.3%). In the add-on to sulfonylurea trials, the incidence of hypoglycemia was 8.6% among the CYCLOSET-treated patients and 5.2% among the placebo-treated patients. In the CYCLOSET safety trial, hypoglycemia was defined as any of the following: 1) symptoms suggestive of hypoglycemia that promptly resolved with appropriate intervention, 2) symptoms with a measured glucose <60 mg/dL or 3) measured glucose below 49 mg/dL regardless of symptoms. In the 52-week safety trial, the incidence of hypoglycemia was 6.9% among the CYCLOSET-treated patients and 5.3% among the placebo-treated patients. In the safety trial, severe hypoglycemia was defined as an inability to self-treat neurological symptoms consistent with hypoglycemia that occurred in the setting of a measured blood glucose <50 mg/dL (or evidence of prompt resolution of these symptoms with administration of oral carbohydrates, subcutaneous glucagon, or intravenous glucose if blood glucose was not measured). In this trial, severe hypoglycemia was reported among 0.5% of CYCLOSET-treated patients and 1% of placebo-treated patients.

Syncope

In clinical trials, syncope was reported in 1.4% of the 2,500 CYCLOSET-treated patients and 0.6% of the 1,454 placebo-treated patients. Among the 3,070 patients studied in the 52-week safety trial, 33 CYCLOSET-treated patients (1.6%) and 7 placebo-treated patients (0.7%) reported syncope. In this trial, electrocardiograms were not available at the time of these events, but an assessment of routine electrocardiograms obtained during the course of the trial did not identify arrhythmias or QTc interval prolongation among the CYCLOSET-treated patients reporting syncope.

Central Nervous System

In the 52-week safety trial, somnolence and hypoesthesia were the only adverse reactions within the nervous system organ class that were reported at a rate of <5% and ≥1% and that occurred at a numerically greater frequency among CYCLOSET-treated patients (CYCLOSET 4.3% vs. placebo 1.3% for somnolence; CYCLOSET 1.4% vs. placebo 1.1% for hypoesthesia).

Fibrotic-Related Complications

Among the CYCLOSET-treated patients (n = 2500) in controlled clinical trials, there was one case (0.04% event rate) of an adverse reaction of pulmonary fibrosis.

Serious Adverse Reactions and Cardiovascular Safety

The primary endpoint of the 52-week safety trial was the occurrence of all serious adverse reactions. A secondary endpoint was the occurrence of the composite of myocardial infarction, stroke, coronary revascularization, hospitalization for angina, and hospitalization for congestive heart failure.

All serious adverse reactions and cardiovascular endpoints were adjudicated by an independent event adjudication committee. Serious adverse reactions occurred in 176/2054 (8.5%) CYCLOSET-treated patients and 98/1016 (9.6%) placebo-treated patients. The hazard ratio comparing CYCLOSET to placebo for the time to first occurrence of a serious adverse reaction was 1.02 (upper bound of one-sided 96% confidence interval, 1.27). None of the serious adverse reactions grouped by System-Organ-Class occurred more than 0.3 percentage points higher with CYCLOSET than with placebo. The composite cardiovascular endpoint occurred in 31 (1.5%) CYCLOSET-treated patients and 30 (3.0%) placebo-treated patients. The hazard ratio comparing CYCLOSET to placebo for the time-to-first occurrence of the prespecified composite cardiovascular endpoint was 0.58 (two-sided 95% confidence interval, 0.35 – 0.96). Therefore, the incidence of this composite endpoint was not increased with CYCLOSET relative to placebo.

6.2 Postmarketing Experience

The following adverse reactions have been identified during post approval use of other formulations of bromocriptine mesylate for indications for which CYCLOSET is not approved (e.g., hyperprolactinemia, acromegaly, and Parkinson's disease), generally at doses higher than those approved for the treatment of type 2 diabetes. Because these reactions are reported voluntarily from a population of uncertain size, it is generally not possible to reliably estimate their frequency or establish a causal relationship to drug exposure.

Hallucinations

Hallucinations and mental confusion including delusions have been reported with bromocriptine.

Fibrotic-Related Complications

Fibrotic complications, including cases of retroperitoneal fibrosis, pulmonary fibrosis, pleural effusion, pleural thickening, pericarditis and pericardial effusions have been reported. These complications do not always resolve when bromocriptine is discontinued. Among several studies investigating a possible relation between bromocriptine exposure and cardiac valvulopathy, some events of cardiac valvulopathy have been reported, but no definitive association between bromocriptine mesylate use and clinically significant (moderate to severe) cardiac valvulopathy could be concluded.

Psychotic and Psychiatric Disorders

Psychotic disorders and impulse control/compulsive behaviors (including pathological gambling) have been reported with bromocriptine.

Adverse Reactions in Postpartum Patients

Serious and life-threatening adverse reactions including hypertension, myocardial infarction, seizures, stroke and psychosis have been reported in postpartum women who were administered bromocriptine for inhibition of lactation.

Neuroleptic-Like Malignant Syndrome

A neuroleptic-like malignant syndrome (manifested by high fever and increase in creatinine phosphokinase) has been reported upon cessation of bromocriptine treatment in patients with advanced Parkinson's disease or patients with secondary Parkinsonism.

7 DRUG INTERACTIONS

- The active ingredient in CYCLOSET (bromocriptine mesylate) is highly bound to serum proteins. Therefore, CYCLOSET may increase the unbound fraction of other concomitantly used highly protein-bound therapies (e.g., salicylates, sulfonamides, chloramphenicol and probenecid), which may alter their effectiveness and risk for side effects.
- CYCLOSET is a dopamine receptor agonist. Concomitant use of dopamine receptor antagonists, such as neuroleptics (e.g., phenothiazines, butyrophenones, thioxanthenes), or metoclopramide may diminish the effectiveness of CYCLOSET, and CYCLOSET may diminish the effectiveness of these other therapies. The concurrent use of CYCLOSET with these agents has not been studied in clinical trials and is not recommended [see Warnings and Precautions (5.5)].
- CYCLOSET in combination with ergot-related drugs may cause an increase in the occurrence of ergot-related side effects, such as nausea, vomiting, and fatigue, and may also reduce the effectiveness of these ergot therapies when used to treat migraine. The concurrent use of these ergot agents within 6 hours of CYCLOSET dosing is not recommended.
- CYCLOSET is extensively metabolized by the liver via CYP3A4. Therefore, potent inhibitors or inducers of CYP3A4 may increase or reduce the circulating levels of CYCLOSET, respectively. Use caution when co-administering drugs that are inhibitors or inducers of CYP3A4. CYCLOSET dose should not exceed 1.6 mg once daily during concomitant use of a moderate CYP3A4 inhibitor (e.g., erythromycin). Concomitant use of strong CYP3A4 inhibitors (e.g., azole antimycotics, HIV protease inhibitors) with CYCLOSET should be avoided. Ensure adequate washout of the strong CYP3A4 inhibitor drug before initiating CYCLOSET treatment [see Clinical Pharmacology (12.3)].
- There are postmarketing reports of hypertension and tachycardia when bromocriptine was co-administered with sympathomimetic drugs (e.g., phenylpropanolamine and isometheptene) in postpartum women. There are limited clinical trial data supporting the safety of co-administering sympathomimetic drugs and CYCLOSET for more than 10 days. Therefore, concomitant use of these agents with CYCLOSET for more than 10 days duration is not recommended. Also, there are limited clinical trial data supporting the safety of selective 5-hydroxytryptamine1B (5-HT1B) agonists (e.g., sumatriptan) used concurrently with CYCLOSET, and the concomitant use of these agents with CYCLOSET should be avoided.

8 USE IN SPECIFIC POPULATIONS

8.1 Pregnancy

Risk Summary

There are no available data on CYCLOSET use in pregnant women with type 2 diabetes. However, prolonged experience with bromocriptine use in pregnant women for other indications over several decades, based on data from published clinical trials, case reports, and epidemiological studies, have not established a drug-associated risk for major birth defects, miscarriage, or adverse maternal or fetal outcomes. Furthermore, only a trace amount of bromocriptine was shown to be transported across the placenta in vitro in a published ex vivo human placental perfusion model. There are risks to the mother and fetus associated with poorly controlled diabetes in pregnancy (see Clinical Considerations). In animal reproduction studies in which bromocriptine mesylate was administered orally during the period of organogenesis, increased prenatal mortality occurred in rats and rabbits at maternally toxic dosages that were more than 24-times the human dose of 4.8 mg/day based on body surface area. No adverse developmental outcomes were observed in monkeys administered bromocriptine mesylate orally during various periods of gestation at doses up to 10-times a human dose of 4.8 mg daily (see Data).

The estimated background risk of major birth defects is 6-10% in women with pre-gestational diabetes with an HbA1c >7 and has been reported to be as high as 20-25% in women with an HbA1c >10. The estimated background risk of miscarriage for the indicated population is unknown. In the U.S. general population, the estimated background risk of major birth defects and miscarriage in clinically recognized pregnancies is 2-4% and 15-20%, respectively.

Clinical Considerations

Disease-Associated Maternal and/or Embryo/Fetal Risk

Poorly controlled diabetes in pregnancy increases the maternal risk for diabetic ketoacidosis, pre-eclampsia, spontaneous abortions, preterm delivery, and delivery complications. Poorly controlled diabetes increases the fetal risk for major birth defects, stillbirth, and macrosomia related morbidity.

Data

Human Data

While available studies cannot definitively establish the absence of risk, data from published studies have not established an association with bromocriptine use during pregnancy and major birth defects, miscarriage, or adverse maternal or fetal outcomes. Available epidemiological studies have methodological limitations including small sample size and inconsistent comparator groups.

Animal Data

Two strains of pregnant rats were dosed orally with 3, 10, and 30 mg/kg/day from Gestation Day (GD) 6-15 and with a single dose of 10 mg/kg on GD 5. Implantation was inhibited at 10 and 30 mg/kg (24 and 72 times the human 4.8 mg daily dose, based on mg/m^2 comparison). When rats were dosed with 3, 10, and 30 mg/kg/day from GD 8-15 there was an increase in resorptions at ≥10 mg/kg. These effects were probably due to the dependence of implantation and maintenance of gestation upon prolactin in the rat and are not clinically relevant as these events in humans are dependent upon luteinizing hormone. There were no drug-related malformations in the rat.

In two strains of pregnant rabbits treated from GD 6-18 with oral doses of 3, 10, 30, 100, and 300 mg/kg/day, there was maternal toxicity and embryolethality (post-implantation loss/early resorptions) at doses ≥10 mg/kg/day (≥48 times the human 4.8 mg daily dose, based on mg/m^2 comparison) and a low incidences of fetal abnormalities at maternally toxic doses ≥ 100 mg/kg/day (≥480 times the human 4.8 mg daily dose, based on mg/m^2 comparison). There were no treatment-related fetal malformations at doses ≤30 mg/kg/day (140 times the human 4.8 mg daily dose, based on mg/m^2 comparison). Implantation was not affected in rabbits treated from GD 1-6 with oral doses of 100-300 mg/kg/day (480-1400 times the human 4.8 mg daily dose, based on mg/m^2 comparison).

In a small study in macaque monkeys given oral doses of 2 mg/kg/day (10 times the human 4.8 mg daily dose, based on mg/m^2 comparison) during organogenesis, no embryotoxic or teratologic effects were observed.

In developmental toxicity studies in monkeys, an oral dose of 0.3 mg/kg administered prior to pregnancy and through GD 30 or 80, or an oral dose of 2 mg/kg administered from GD 20-24, resulted in no embryotoxicity (doses up to 10 times the human 4.8 mg daily dose based on mg/m^2 comparison).

8.2 Lactation

Risk Summary

CYCLOSET is contraindicated in lactating patients because its active ingredient, bromocriptine, inhibits lactation. In addition, serious and life-threatening adverse reactions including hypertension, myocardial infarction, seizures, stroke, and psychosis have been reported postmarketing in postpartum women who were administered bromocriptine for inhibition of lactation. The indication for use of bromocriptine for inhibition of lactation was withdrawn from bromocriptine-containing products and is not approved for CYCLOSET [see Warnings and Precautions (5.7), Adverse Reactions (6.2)].

8.4 Pediatric Use

The safety and effectiveness of CYCLOSET in pediatric patients have not been established.

8.5 Geriatric Use

In the two clinical trials of CYCLOSET add-on to sulfonylurea therapy and in the monotherapy trial, a total of 54 patients randomized to CYCLOSET were ≥65 years old. In the 52-week safety trial, 601 of the 2,054 CYCLOSET-treated patients (29%) were ≥65 years old. No overall differences in safety or effectiveness were observed between the elderly and younger patients, but greater sensitivity of some older individuals cannot be ruled out [See Clinical Studies (14)].

10 OVERDOSAGE

With another formulation of bromocriptine mesylate, the most commonly reported signs and symptoms associated with acute overdose were nausea, vomiting, constipation, diaphoresis, dizziness, pallor, severe hypotension, malaise, confusion, lethargy, drowsiness, delusions, hallucinations, and repetitive yawning. The lethal dose has not been established.

Treatment of overdose consists of removal of the drug by emesis (if conscious), gastric lavage, activated charcoal, or saline catharsis. Careful supervision and recording of fluid intake and output is essential. Hypotension should be treated by placing the patient in the Trendelenburg position and administering intravenous fluids. If satisfactory relief of hypotension cannot be achieved by using the above measures to their fullest extent, vasopressors should be considered.

11 DESCRIPTION

CYCLOSET Tablets contain micronized bromocriptine mesylate, an ergot derivative. Bromocriptine mesylate is chemically designated [Ergotaman-3',6',18-trione, 2-bromo-12'-hydroxy-2'-(1-methylethyl)-5'-(2-methylpropyl)-, monomethanesulfonate (salt), (5'α)-]. CYCLOSET is a single enantiomer with absolute configuration 5R, 8R, 2'R, 5'S, 11'S, 12'S.

The structural formula of bromocriptine is shown below:

Bromocriptine mesylate in CYCLOSET is a white or slightly colored micronized crystalline powder with a molecular formula of C32H40BrN5O5∙CH4SO3 and a molecular weight of 750.72. CYCLOSET Tablets contain bromocriptine mesylate USP in an amount equivalent to 0.8 mg. of bromocriptine. Each tablet contains the following inactive ingredients: lactose, corn starch, magnesium stearate, colloidal silicon dioxide, and citric acid.

12 CLINICAL PHARMACOLOGY

12.1 Mechanism of Action

CYCLOSET contains bromocriptine mesylate, a sympatholytic, dopamine D2 receptor agonist. In patients with type 2 diabetes, timed morning administration of CYCLOSET is associated with increased insulin sensitivity and glucose disposal and reduced fasting and postprandial hyperglycemia throughout the meals of the day without raising plasma insulin levels.

12.2 Pharmacodynamics

Postprandial Glucose and Insulin Response to a Meal

Patients with type 2 diabetes and inadequate glycemic control on diet alone were randomized to CYCLOSET or placebo in a 24-week monotherapy clinical trial. At baseline and study end, plasma samples for insulin and glucose were obtained before and 1 hour, and 2 hours after standardized meals for breakfast, lunch, and dinner. In this trial, once-daily (8 a.m.) CYCLOSET improved postprandial glucose without increasing plasma insulin concentrations.

Insulin-Mediated Glucose Disposal

Patients with type 2 diabetes and inadequate glycemic control on sulfonylurea therapy were randomized to CYCLOSET or placebo in a 16-week clinical trial. In this trial CYCLOSET therapy improved insulin-mediated glucose disposal and glucose tolerance and resulted in lower plasma glucose and HbA1c levels.

12.3 Pharmacokinetics

Absorption and Bioavailability

When administered orally, approximately 65-95% of the CYCLOSET dose of bromocriptine mesylate is absorbed. Due to extensive first-pass metabolism, approximately 7% of the dose reaches the systemic circulation. Under fasting conditions the time to maximum plasma concentration is 53 minutes. In contrast, following a standard high-fat meal, the time to maximum plasma concentration is increased to approximately 90-120 minutes. Also, the relative bioavailability of CYCLOSET is increased under fed as compared to fasting conditions by an average of approximately 55-65% (increase in AUCinf).

Distribution

Bromocriptine is 90-96% bound to plasma proteins. The volume of distribution is approximately 61 L.

Metabolism

Bromocriptine mesylate is extensively metabolized in the gastrointestinal tract and liver. Metabolism by CYP3A4 is the major metabolic pathway. Most of the absorbed dose (approximately 93%) undergoes first-pass metabolism. The remaining 7% reaches the systemic circulation.

Excretion

The major route of excretion of bromocriptine is in the bile with the remaining approximately 2-6% of an oral dose excreted via the urine. The elimination half-life is approximately 6 hours. Prior consumption of a standard high-fat meal has little to no effect on the elimination half-life of CYCLOSET.

Specific Populations

Renal Impairment

No pharmacokinetic studies have been conducted in patients with renal impairment. Although the kidney is a minor pathway for elimination of CYCLOSET, caution should be used in patients with renal impairment.

Hepatic Impairment

No pharmacokinetic studies have been conducted in patients with hepatic impairment. Because CYCLOSET is predominantly metabolized by the liver, caution should be used in patients with hepatic impairment.

Gender

The plasma exposure of CYCLOSET is increased 18-30% in females compared to males.

Geriatric

No pharmacokinetic studies have been conducted in geriatric subjects.

Pediatric

Studies characterizing the pharmacokinetics of CYCLOSET in pediatric patients have not been performed.

Race

Studies characterizing the pharmacokinetics of CYCLOSET among different ethnic groups have not been performed.

Drug Interactions

In Vitro Assessment

Although bromocriptine is a competitive inhibitor of CYP3A4, in vivo drug interaction potential is low because the inhibitory potency for CYP3A4 is approximately 10,000-fold higher than the maximum plasma levels reached in vivo (Cmax of approximately 80-125 pg/mL) following a 4.8 mg oral dose of CYCLOSET.

Agents inducing CYP3A4 activity such as rifampin or dexamethasone would be expected to decrease CYCLOSET plasma levels. There was no significant in vitro inhibition of other major CYP450 enzymes (1A2, 2C9/19, 2D6) by bromocriptine.

In Vivo Assessment

The concomitant use of macrolide antibiotics such as erythromycin (250 mg four times a day), a known inhibitor of CYP3A4, along with bromocriptine (5 mg) was shown to increase the AUC (2.8-fold) and Cmax (4.6-fold) of bromocriptine [see Dosage and Administration (2.3), Drug Interactions (7)].

13 NONCLINICAL TOXICOLOGY

13.1 Carcinogenesis, Mutagenesis, Impairment of Fertility

Carcinogenesis

In a 74-week dietary study in mice at doses up to 50 mg/kg/day (60 times the human 4.8 mg daily dose, based on mg/m^2 comparison), there was no evidence of tumorigenicity.

In a 100-week dietary carcinogenicity study in rats at doses of 1.8, 9.9 and 44.5 mg/kg/day (up to 107 times the human 4.8 mg daily dose, based on mg/m^2 comparison), there was a significant increase in the incidence of malignant uterine neoplasms at ≥9.9 mg/kg/day (≥24-times the human 4.8 mg daily dose, based on mg/m^2 comparison). The increase in uterine neoplasms was probably due to the inhibition of prolactin-stimulated progesterone secretion resulting in estrogen domination and endometrial stimulation in the aging rat. Because prolactin does not play a role in human progesterone production, this finding is unlikely to be clinically relevant.

Mutagenicity

Bromocriptine was not mutagenic in the in vitro Ames bacterial mutation assay, the V79 Chinese hamster fibroblast mutagenicity test, the in vivo bone marrow micronucleus test in mice and the in vivo Chinese hamster bone marrow chromosomal aberration test.

Impairment of Fertility

There was no effect on fertility in female rats treated with oral doses of 1 and 3 mg/kg (2 to 7 times the human 4.8 mg daily dose, based on mg/m^2 comparison) from two weeks prior to mating through two weeks post mating or throughout lactation. Postnatal pup weight gain was reduced dose-dependently in treated groups, probably due to lactation inhibition.

In male rats administered oral doses of 2, 10, and 50 mg/kg/day (up to 120 times the human 4.8 mg daily dose, based on mg/m^2 comparison) that were mated with untreated females, there was no effect on mating or fertility. However, there was a slight increase in postnatal (post-partum days 0-21) pup mortality in the 10 and 50 mg/kg/day groups (24-120 times the human 4.8 mg daily dose, based on mg/m^2 comparison).

14 CLINICAL STUDIES

A total of 3,723 patients with type 2 diabetes were randomized across 4 double-blind, placebo-controlled clinical trials conducted to evaluate the safety and glycemic efficacy of CYCLOSET. In the pooled 24-week monotherapy trial and the two 24-week add-on to sulfonylurea trials (N = 653), the mean age of the CYCLOSET-treated patients (N = 324) was 55 years, 71% were male and 73% Caucasian. In the 52-week safety trial (N = 3,070), the mean age for the entire study population was 60 years and 43% of patients were female, 68% were Caucasian, 17% were Black, 13% were Hispanic, and 1% were Asian.

In all 4 clinical trials, patients assigned to treatment with CYCLOSET received an initial dose of 0.8 mg, which was increased by 0.8 mg each week for 6 weeks (4.8 mg/day final dose) if no intolerance occurred or until the maximum tolerated dose ≥1.6 mg/day was reached. In patients with type 2 diabetes, treatment with CYCLOSET produced clinically significant improvements in HbA1c and postprandial glucose (PPG).

14.1 Monotherapy

A total of 159 adults with type 2 diabetes, overweight (body mass index ≥26.0 kg/m^2 for males and ≥28.0 kg/m^2 for females), and inadequate glycemic control (HbA1c 7.5-11%) participated in a 24-week, placebo-controlled, monotherapy trial that evaluated the efficacy and safety of CYCLOSET as an adjunct to diet and exercise. Mean body weight at baseline was 93 kg in the CYCLOSET group and 96 kg in the placebo group. Mean HbA1c at baseline was 9.0% in the CYCLOSET group and 8.8% in the placebo group. Mean duration of diabetes at baseline was 5 years in the CYCLOSET group and 4 years in the placebo group. Of the 80 patients in the CYCLOSET group, 69% (N = 55) achieved the maximum daily dose of 4.8 mg. CYCLOSET improved HbA1c and fasting plasma glucose compared to placebo (Table 2). Mean change from baseline in body weight was +0.2 kg in the CYCLOSET group (N = 78) and +0.5 kg in the placebo group (N = 77).

Table 2: Changes in Glycemic Parameters in a 24-Week Placebo-Controlled Study of CYCLOSET as Monotherapy in Patients with Type 2 Diabetes [intent-to-treat population with last observation carried forward]
 | CYCLOSET N = 80 (1.6 - 4.8 mg) | Placebo N = 79
HbA1c (%) | N = 74 | N = 74
Baseline (mean) | 9.0 | 8.8
Change from baseline (adj. mean) | -0.1 | 0.3
Difference from placebo (adj. mean) | -0.4 [p = 0.05]
Fasting Plasma Glucose (mg/dL) | N = 76 | N = 75
Baseline (mean) | 215 | 205
Change from baseline (adj. mean) | 0 | 23
Difference from placebo (adj. mean) | -23 [p = 0.005]
P-value calculated by ANOVA

14.2 Combination Therapy

CYCLOSET Add-on to Sulfonylurea Therapy

Patients with type 2 diabetes and inadequate glycemic control (HbA1c 7.8-12.5%) on sulfonylurea therapy (mean HbA1c 9.4%) participated in Study L, a 24-week, randomized, double-blind, placebo-controlled trial that evaluated the safety and glycemic efficacy of CYCLOSET when added to stable sulfonylurea therapy. The mean duration of diabetes was 6 years in the CYCLOSET group and 8 years in the placebo group. The range of body mass index was 26-40 kg/m^2 for men and 28-40 kg/m^2 for women, with a mean of 32 kg/m^2 in both treatment groups. Of the 122 patients in the CYCLOSET group, 83 (68%) achieved the maximum dose of study drug. The mean change from baseline in body weight was +0.9 kg in the CYCLOSET group and +0.5 kg in the placebo group.

In another similarly designed trial, Study K, patients with type 2 diabetes and inadequate glycemic control (HbA1c 7.8-12.5 %) on stable sulfonylurea therapy were randomized to add-on therapy with either CYCLOSET (N = 122) or placebo (N = 123). The range of body mass index was 26-40 kg/m^2 for men and 28-40 kg/m^2 for women, with a mean of 32 kg/m^2 in the CYCLOSET group and 33 kg/m^2 in the placebo group. Of the 122 patients in the CYCLOSET group, 91 (75%) achieved the maximum dose of study drug. Mean change from baseline in body weight was +1.4 kg in the CYCLOSET group and +0.5 kg in the placebo group. CYCLOSET improved HbA1c and fasting blood glucose concentrations compared to placebo (Table 3).

Table 3: Changes in Glycemic Parameters for CYCLOSET Versus Placebo in Two Add-on to Sulfonylurea Trials
 | Study K [intent-to-treat population using last observation carried forward between-group change from baseline in HbA1c] |  | Study L
 | CYCLOSET Add-on to Sulfonylurea N = 122 | Placebo Add-on to Sulfonylurea N = 123 | CYCLOSET Add-on to Sulfonylurea N = 122 | Placebo Add-on to Sulfonylurea N = 127
HbA1c (%) | n = 114 | n = 122 | n = 114 | n = 123
Baseline (mean) | 9.3 | 9.4 | 9.3 | 9.4
Change from baseline (adj. mean) | -0.1 | 0.4 | -0.4 | 0.3
Difference from placebo (adj. mean) | -0.5 [p≤ 0.001] |  | -0.6
Fasting Plasma Glucose (mg/dL) | n = 116 | n = 119 | n = 113 | n = 123
Baseline (mean) | 216 | 227 | 220 | 226
Change from baseline (adj. mean) | 10 | 28 | 3 | 23
Difference from placebo (adj. mean) | -18 [p = 0.02] |  | -20 [p = 0.006]
P-value calculated by ANOVA

CYCLOSET Add-on to Various Oral Antidiabetic Agents

Patients with type 2 diabetes receiving various antidiabetic therapies (mean baseline HbA1c 8.3%) participated in a 52-week randomized, double-blind, placebo-controlled safety trial [see Adverse Reactions (6.1)]. The daily CYCLOSET dose was initiated at 0.8 mg and increased by 0.8 mg each week for 6 weeks if no intolerance occurred or until the maximum tolerated dose ≥1.6 mg/day was reached. Approximately 70% of patients assigned to treatment with CYCLOSET reached the maximum daily dose of 4.8 mg. Physicians were instructed to adjust the dosage of concomitant diabetes therapies to avert hypoglycemia or uncontrolled hyperglycemia. Doses of background antidiabetic medications could be adjusted at any time during the trial and additional antidiabetic medications were permitted after week 12, if needed to maintain ideal glycemic control. Mean baseline HbA1c was 7.0% in both treatment groups. The least-squares mean change in HbA1c from baseline to week 24 was 0.0% with CYCLOSET (N = 2049) and +0.2% with placebo (N = 1015). Because many patients (60%) were already at treatment goal at baseline (HbA1c <7%), pre-specified subgroup analyses of glycemic efficacy (change in HbA1c from baseline to week 24) were conducted for patients who had inadequate glycemic control (baseline HbA1c ≥7.5%) on 1-2 oral antidiabetic therapies at the time of study entry. Patients receiving CYCLOSET, compared to placebo, experienced a significant improvement in HbA1c when used as adjunctive therapy to 1-2 oral antidiabetic medications, including the subgroup of patients treated only with background metformin + sulfonylurea (Table 4). The mean change in body weight for the glycemic efficacy subgroup (N = 559) from baseline to week 24 was -0.1 kg with CYCLOSET and +0.1 kg. The mean change in body weight for the entire study population (N = 3070) from baseline to week 52 was +0.2 kg with CYCLOSET and +0.1 kg with placebo.

Table 4: Changes in HbA1c from Baseline to Week 24 in the CYCLOSET Safety Trial Subgroup of Patients with Type 2 Diabetes and Inadequate Glycemic Control (Baseline HbA1c ≥7.5%) on 1-2 Oral Antidiabetic Medications [intent-to-treat population using last observation carried forward between-group change from baseline in HbA1c]
 | 24-Week Intent-to-Treat
 | CYCLOSET | Placebo
Adjunct to 1-2 Oral Antidiabetic Medications | N = 376 | N = 183
HbA1c (%)
Baseline mean | 8.3 | 8.4
Change from baseline (adjusted mean) | -0.4 | 0.0
Difference from placebo (adjusted mean) | -0.5 [p<0.001]
% Patients achieving HbA1c of ≤7.0 | 25 | 9
Adjunct to Metformin + Sulfonylurea Only [patients in the "metformin + sulfonylurea only" subgroup are also counted in the "adjunct to 1-2 oral antidiabetic medications" subgroup] | N = 177 | N = 90
HbA1c (%)
Baseline mean | 8.3 | 8.3
Change from baseline (adjusted mean) | -0.5 | 0.0
Difference from placebo (adjusted mean) | -0.5
% Patients achieving HbA1c of ≤7.0 | 27 | 9
P-value is based on an ANCOVA model with treatment and center as fixed effects, and baseline HbA1c as covariates

14.3 Changes in Lipids and Blood Pressure

CYCLOSET does not have an unfavorable effect on fasting plasma lipids.

CYCLOSET has not demonstrated an unfavorable hypertensive effect on blood pressure. Hypotension has been reported with use of CYCLOSET in clinical trials [see Warnings and Precautions (5.1)].

16 HOW SUPPLIED/STORAGE AND HANDLING

CYCLOSET 0.8 mg tablets are WHITE and round with "C" on one side and "9" on the other.

The tablets are supplied as follows:
NDC 73515-123-30 unit-of-use bottles of 200
NDC 73515-123-21 unit-of-use bottles of 21 (samples only).

Storage

Store and dispense: At 20-25°C (68-77°F) in a tight, light-resistant container. See USP Controlled Room Temperature.

17 PATIENT COUNSELING INFORMATION

Advise the patient to read the FDA-approved patient labeling (Patient Information).

Hypotension

Advise patients that they may develop postural (orthostatic) hypotension with or without symptoms such as dizziness, nausea, and diaphoresis. Hypotension and syncope may occur more frequently during initial therapy or with an increase in dose at any time. During early treatment with CYCLOSET, advise patients to make slow postural changes and to avoid situations that could predispose to serious injury if syncope was to occur [see Warnings and Precautions (5.1)].

Impulse Control/Compulsive Behaviors

Advise patients that they may experience impulse control and/or compulsive behaviors while taking CYCLOSET and to inform their physician or healthcare provider if they develop new or increased gambling urges, sexual urges, uncontrolled spending, binge or compulsive eating, or other urges while being treated with CYCLOSET [see Warnings and Precautions (5.3)].

Somnolence

Advise patients that CYCLOSET may cause somnolence. Advise patients not to operate heavy machinery if symptoms of somnolence occur [see Warnings and Precautions (5.4)].

Pregnancy and Lactation

Advise patients not to take CYCLOSET postpartum or while lactating [see Warnings and Precautions (5.7), Use in Specific Populations (8.2)]. Serious and life-threatening adverse reactions including hypertension, myocardial infarction, seizures, stroke and psychosis have been reported in postpartum women who were administered bromocriptine for inhibition of lactation.

Missed Doses

Advise patients to take CYCLOSET within 2 hours after waking in the morning. If the morning dose is missed, instruct patients to take their usual dose the following morning. Doses of CYCLOSET should not be doubled the following morning.

Manufactured for:
VeroScience, LLC
Tiverton, RI 02878 USA

Distributed by:
Avvisto Therapeutics, LLC
Tiverton, RI 02878 USA

Printed in USA

For information for healthcare professionals, call 1-888-621-1215.

For patent information: http://veroscience.com/products/patents.html

Cycloset is a registered trademark of VeroScience LLC, Tiverton, RI 02878 USA used under license.

Patient Information
CYCLOSET® (Sikloset)
(bromocriptine mesylate tablets)
for oral use

Read this Patient Information that comes with CYCLOSET before you start taking it and each time you get a refill. There may be new information. This information does not take the place of talking with your healthcare provider about your medical condition or treatment.

What is CYCLOSET?

- CYCLOSET is a prescription medicine used with diet and exercise to lower blood sugar in adults with type 2 diabetes.
- CYCLOSET is not for people with type 1 diabetes.
- CYCLOSET is not for people with diabetic ketoacidosis.
- It is not known if CYCLOSET is safe and effective in children.

Who should not take CYCLOSET?

Do not take CYCLOSET if you:

- are allergic to bromocriptine or any of the ingredients in CYCLOSET. See the end of this Patient Information leaflet for a complete list of ingredients in CYCLOSET.
- are allergic to ergot medicines. Ask your healthcare provider for a list of these medicines, if you are not sure.
- have fainting (syncopal) migraine headaches.
- are a woman who has recently given birth to a child (postpartum). CYCLOSET can cause serious and life-threatening problems including high blood pressure (hypertension), heart attack, seizures, stroke and psychosis (losing touch with reality).
- are breastfeeding.

Talk to your healthcare provider before taking CYCLOSET if you have any of these conditions.

What should I tell my healthcare provider before taking CYCLOSET?

Before taking CYCLOSET, tell your healthcare provider about all of your medical conditions, including if you:

- have ever passed out (fainted).
- have migraine headaches.
- have or have had low blood pressure (hypotension).
- take medicines for high blood pressure (hypertension).
- have or have had a mental health problem, especially a psychotic disorder.
- are pregnant or plan to become pregnant. It is not known if CYCLOSET will harm your unborn baby. If you are pregnant, talk with your healthcare provider about the best way to control your blood sugar while you are pregnant.

Tell your healthcare provider about all the medicines you take, including prescription and over-the-counter medicines, vitamins, and herbal supplements.

Especially tell your healthcare provider if you take:

- medicines for mental health problems, especially anti-psychotic medicines called dopamine receptor antagonists
- medicines for migraine or other types of headaches
- other medicines that work like CYCLOSET (dopamine receptor agonists) to treat conditions such as Parkinson's disease, high levels of a hormone called prolactin in your blood (hyperprolactinemia), restless leg syndrome and too much growth hormone (acromegaly)
- medicines for type 2 diabetes

Ask your healthcare provider or pharmacist for a list of these medicines if you are not sure.

CYCLOSET may affect the way other medicines work, and other medicines may affect how CYCLOSET works.

Know the medicines you take. Keep a list of your medicines and show it to your healthcare provider and pharmacist when you get a new medicine.

How should I take CYCLOSET?

- Take CYCLOSET exactly as your healthcare provider tells you to take it.
- Take CYCLOSET by mouth each morning with food.
- Take CYCLOSET within 2 hours after waking in the morning.
- If you miss your morning dose, wait until the next morning to take your medication. Do not take a double dose of CYCLOSET.
- During periods of stress on the body, such as fever, trauma, infection, or surgery, your medication needs may change. Contact your healthcare provider right away as your medication needs change.
- If you take too much CYCLOSET, call your healthcare provider or go to the nearest emergency department right away.
- While taking CYCLOSET:
  - check your blood sugar as your healthcare provider tells you to
  - stay on your prescribed diet and exercise program
  - talk to your doctor about how to prevent, recognize, and manage low blood sugar (hypoglycemia), high blood sugar (hyperglycemia), and complications of diabetes
  - see your healthcare provider for regular blood tests, including your blood sugar levels and hemoglobin A1C

What are the possible side effects of CYCLOSET?

CYCLOSET may cause serious side effects, including:

- Low blood pressure (hypotension) including low blood pressure when you suddenly change positions (orthostatic hypotension). This can happen more often when first starting CYCLOSET or if your dose is increased. Symptoms of low blood pressure when you suddenly change positions can include dizziness, nausea, sweating, fainting or light-headedness. Stand up slowly when moving from a sitting or lying position. You should avoid activities that could cause injury if you feel light-headed or faint.
- Feeling tired and sleepy (somnolence). Tiredness and sleepiness can happen with CYCLOSET, especially when first starting CYCLOSET. Tiredness and sleepiness are common but can also be serious. If you feel tired and sleepy while taking CYCLOSET, you should not drive or operate heavy machinery.
- Uncontrollable (compulsive) behaviors. CYCLOSET is in a class of medicines that may cause some people to get urges to behave in a way that may be unusual for them. Examples of these behaviors include strong urges to gamble, increased sexual urges, strong urges to spend money, binge eating or eating that you cannot control. If you or your family members notice that you are developing any unusual behaviors, talk to your healthcare provider. These behaviors may go away if your dose of CYCLOSET is lowered or stopped.
- Serious and life-threatening problems in women who have recently given birth to a child (postpartum). See "Who should not take CYCLOSET?"

The most common side effects of CYCLOSET include:

- nausea

- headache

- dizziness

- vomiting

Tell your healthcare provider if you have any side effect that bothers you or that does not go away.

These are not all the possible side effects of CYCLOSET. For more information, ask your healthcare provider or pharmacist.

Call your doctor for medical advice about side effects. You may report side effects to FDA at 1-800-FDA-1088.

How should I store CYCLOSET?

- Store CYCLOSET at room temperature between 68°F and 77°F (20°C and 25°C).
- Store CYCLOSET in a tight, light resistant container.

Keep CYCLOSET and all medicines out of the reach of children.

General information about the safe and effective use of CYCLOSET.

Medicines are sometimes prescribed for purposes other than those listed in a Patient Information leaflet. Do not use CYCLOSET for a condition for which it was not prescribed. Do not give CYCLOSET to other people, even if they have the same symptoms that you have. It may harm them.

This leaflet summarizes the most important information about CYCLOSET. If you would like more information, talk with your healthcare provider. You can ask your healthcare provider or pharmacist for information about CYCLOSET that is written for health professionals.

What are the ingredients in CYCLOSET?

Active ingredient: bromocriptine mesylate

Inactive ingredients: lactose, corn starch, magnesium stearate, colloidal silicon dioxide, and citric acid

Manufactured for:
VeroScience, LLC
Tiverton, RI 02878

Distributed by:
Avvisto Therapeutics, LLC
Tiverton, RI 02878 USA

For information for healthcare professionals, call 1-888-621-1215.

CYCLOSET is a registered trademark of:
VeroScience, LLC
Tiverton, RI 02878

For more information, go to www.CYCLOSET.com or call 1-888-621-1215.

This Patient Information has been approved by the U.S. Food and Drug Administration.

Revised: 08/2020

PRINCIPAL DISPLAY PANEL - 0.8 mg Tablet Bottle Label

NDC 73515-123-30

CYCLOSET®
bromocriptine mesylate tablets

0.8 mg

200 Tablets
Rx only